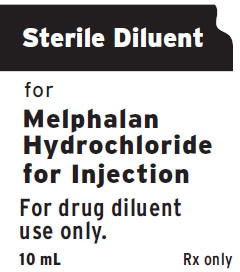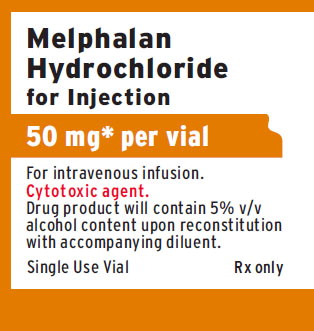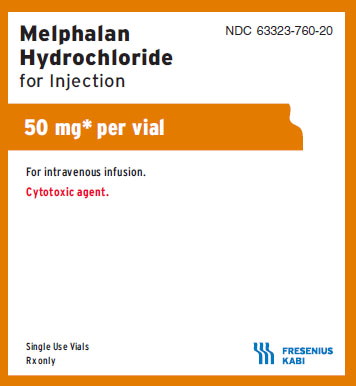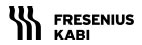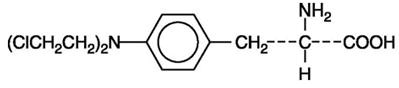 DRUG LABEL: Melphalan
NDC: 63323-760 | Form: KIT | Route: INTRAVENOUS
Manufacturer: Fresenius Kabi USA, LLC
Category: prescription | Type: HUMAN PRESCRIPTION DRUG LABEL
Date: 20260114

ACTIVE INGREDIENTS: MELPHALAN HYDROCHLORIDE 50 mg/10 mL
INACTIVE INGREDIENTS: POVIDONE, UNSPECIFIED; SODIUM CITRATE, UNSPECIFIED FORM; PROPYLENE GLYCOL; ALCOHOL; WATER

Melphalan Hydrochloride for Injection

Rx only

WARNING
Melphalan should be administered under the supervision of a qualified physician experienced in the use of cancer chemotherapeutic agents. Severe bone marrow suppression with resulting infection or bleeding may occur. Controlled trials comparing intravenous (IV) to oral melphalan have shown more myelosuppression with the IV formulation. Hypersensitivity reactions, including anaphylaxis, have occurred in approximately 2% of patients who received the IV formulation. Melphalan is leukemogenic in humans. Melphalan produces chromosomal aberrations in vitro and in vivo and, therefore, should be considered potentially mutagenic in humans.

DESCRIPTION:

Melphalan, also known as L-phenylalanine mustard, phenylalanine mustard, L-PAM, or L-sarcolysin, is a phenylalanine derivative of nitrogen mustard. Melphalan is a bifunctional alkylating agent that is active against selected human neoplastic diseases. It is known chemically as 4-[bis(2-chloroethyl) amino]-L-phenylalanine. The structural formula is:

C13 H18 Cl2 N2 O2 M.W. 305.20

Melphalan is the active L-isomer of the compound and was first synthesized in 1953 by Bergel and Stock; the D-isomer, known as medphalan, is less active against certain animal tumors, and the dose needed to produce effects on chromosomes is larger than that required with the L-isomer. The racemic (DL-) form is known as merphalan or sarcolysin.

Melphalan is practically insoluble in water and has a pKa1 of approximately 2.5.

Melphalan hydrochloride for injection is supplied as a sterile, nonpyrogenic, freeze-dried powder. Each single use vial contains melphalan hydrochloride equivalent to 50 mg melphalan and 20 mg povidone. Melphalan hydrochloride for injection is reconstituted using the sterile diluent provided. Each vial of sterile diluent contains sodium citrate 0.2 g, propylene glycol 6 mL, ethanol (100%) 0.5 mL, and water for injection to a total of 10 mL. Melphalan hydrochloride is administered intravenously.

CLINICAL PHARMACOLOGY:

Melphalan is an alkylating agent of the bischloroethylamine type. As a result, its cytotoxicity appears to be related to the extent of its interstrand cross-linking with DNA, probably by binding at the N^7 position of guanine. Like other bifunctional alkylating agents, it is active against both resting and rapidly dividing tumor cells.

Pharmacokinetics

Following injection, drug plasma concentrations declined rapidly in a biexponential manner with distribution phase and terminal elimination phase half-lives of approximately 10 and 75 minutes, respectively. Estimates of average total body clearance varied among studies, but typical values of approximately 7 to 9 mL/min/kg (250 to 325 mL/min/m^2) were observed. One study has reported that on repeat dosing of 0.5 mg/kg every 6 weeks, the clearance of melphalan decreased from 8.1 mL/min/kg after the first course, to 5.5 mL/min/kg after the third course, but did not decrease appreciably after the third course. Mean (±SD) peak melphalan plasma concentrations in myeloma patients given IV melphalan at doses of 10 or 20 mg/m^2 were 1.2 ± 0.4 and 2.8 ± 1.9 mcg/mL, respectively.

The steady-state volume of distribution of melphalan is 0.5 L/kg. Penetration into cerebrospinal fluid (CSF) is low. The average melphalan binding to plasma proteins is highly variable (range: 53% to 92%). Serum albumin is the major binding protein, accounting for approximately 40% to 60% of the plasma protein binding, while α1-acid glycoprotein accounts for about 20% of the plasma protein binding. Approximately 30% of melphalan is (covalently) irreversibly bound to plasma proteins. Interactions with immunoglobulins have been found to be negligible.

Melphalan is eliminated from plasma primarily by chemical hydrolysis to monohydroxymelphalan and dihydroxymelphalan. Aside from these hydrolysis products, no other melphalan metabolites have been observed in humans. Although the contribution of renal elimination to melphalan clearance appears to be low, one study noted an increase in the occurrence of severe leukopenia in patients with elevated BUN after 10 weeks of therapy.

Clinical Trial

A randomized trial compared prednisone plus IV melphalan to prednisone plus oral melphalan in the treatment of myeloma. As discussed below, overall response rates at week 22 were comparable; however, because of changes in trial design, conclusions as to the relative activity of the 2 formulations after week 22 are impossible to make.

Both arms received oral prednisone starting at 0.8 mg/kg/day with doses tapered over 6 weeks. Melphalan doses in each arm were:
Arm 1: Oral melphalan 0.15 mg/kg/day x 7 followed by 0.05 mg/kg/day when WBC began to rise.

Arm 2: IV melphalan 16 mg/m^2 q 2 weeks x 4 (over 6 weeks) followed by the same dose every 4 weeks.
Doses of melphalan were adjusted according to the following criteria:

Table 1. Criteria for Dosage Adjustment in a Randomized Clinical Trial

WBC/mm^3 | Platelets | Percent of Full Dose
≥ 4,000 | ≥ 100,000 | 100
≥ 3,000 | ≥ 75,000 | 75
≥ 2,000 | ≥ 50,000 | 50
< 2,000 | < 50,000 | 0

One hundred seven patients were randomized to the oral melphalan arm and 203 patients to the IV melphalan arm. More patients had a poor-risk classification (58% versus 44%) and high tumor load (51% versus 34%) on the oral compared to the IV arm (P < 0.04). Response rates at week 22 are shown in the following table:

Table 2. Response Rates at Week 22

Initial Arm | Evaluable Patients | Responders n (%) | P
Oral melphalan | 100 | 44 (44%) | P > 0.2
IV melphalan | 195 | 74 (38%) | P > 0.2

Because of changes in protocol design after week 22, other efficacy parameters such as response duration and survival cannot be compared.

Severe myelotoxicity (WBC ≤ 1,000 and/or platelets ≤ 25,000) was more common in the IV melphalan arm (28%) than in the oral melphalan arm (11%).

An association was noted between poor renal function and myelosuppression; consequently, an amendment to the protocol required a 50% reduction in IV melphalan dose if the BUN was ≥ 30 mg/dL. The rate of severe leukopenia in the IV arm in the patients with BUN over 30 mg/dL decreased from 50% (8/16) before protocol amendment to 11% (3/28) (P = 0.01) after the amendment.

Before the dosing amendment, there was a 10% (8/77) incidence of drug-related death in the IV arm. After the dosing amendment, this incidence was 3% (3/108). This compares to an overall 1% (1/100) incidence of drug-related death in the oral arm.

INDICATIONS AND USAGE:

Melphalan hydrochloride for injection is indicated for the palliative treatment of patients with multiple myeloma for whom oral therapy is not appropriate.

CONTRAINDICATIONS:

Melphalan should not be used in patients whose disease has demonstrated prior resistance to this agent. Patients who have demonstrated hypersensitivity to melphalan should not be given the drug.

WARNINGS:

Melphalan hydrochloride may cause local tissue damage should extravasation occur, and consequently it should not be administered by direct injection into a peripheral vein. It is recommended that melphalan hydrochloride for injection be administered by injecting slowly into a fast-running IV infusion via an injection port, or via a central venous line (see DOSAGE AND ADMINISTRATION, Administration Precautions).

Melphalan should be administered in carefully adjusted dosage by or under the supervision of experienced physicians who are familiar with the drug’s actions and the possible complications of its use.

As with other nitrogen mustard drugs, excessive dosage will produce marked bone marrow suppression. Bone marrow suppression is the most significant toxicity associated with melphalan hydrochloride in most patients. Therefore, the following tests should be performed at the start of therapy and prior to each subsequent dose of melphalan hydrochloride: platelet count, hemoglobin, white blood cell count, and differential. Thrombocytopenia and/or leukopenia are indications to withhold further therapy until the blood counts have sufficiently recovered. Frequent blood counts are essential to determine optimal dosage and to avoid toxicity. Dose adjustment on the basis of blood counts at the nadir and day of treatment should be considered.

Hypersensitivity reactions including anaphylaxis have occurred in approximately 2% of patients who received the IV formulation (see ADVERSE REACTIONS). These reactions usually occur after multiple courses of treatment. Treatment is symptomatic. The infusion should be terminated immediately, followed by the administration of volume expanders, pressor agents, corticosteroids, or antihistamines at the discretion of the physician. If a hypersensitivity reaction occurs, IV or oral melphalan should not be readministered since hypersensitivity reactions have also been reported with oral melphalan.

Carcinogenesis

Secondary malignancies, including acute nonlymphocytic leukemia, myeloproliferative syndrome, and carcinoma, have been reported in patients with cancer treated with alkylating agents (including melphalan). Some patients also received other chemotherapeutic agents or radiation therapy. Precise quantitation of the risk of acute leukemia, myeloproliferative syndrome, or carcinoma is not possible. Published reports of leukemia in patients who have received melphalan (and other alkylating agents) suggest that the risk of leukemogenesis increases with chronicity of treatment and with cumulative dose. In one study, the 10-year cumulative risk of developing acute leukemia or myeloproliferative syndrome after oral melphalan therapy was 19.5% for cumulative doses ranging from 730 to 9,652 mg. In this same study, as well as in an additional study, the 10-year cumulative risk of developing acute leukemia or myeloproliferative syndrome after oral melphalan therapy was less than 2% for cumulative doses under 600 mg. This does not mean that there is a cumulative dose below which there is no risk of the induction of secondary malignancy. The potential benefits from melphalan therapy must be weighed on an individual basis against the possible risk of the induction of a second malignancy.

Adequate and well-controlled carcinogenicity studies have not been conducted in animals. However, intraperitoneal (IP) administration of melphalan in rats (5.4 to 10.8 mg/m^2) and in mice (2.25 to 4.5 mg/m^2) 3 times per week for 6 months followed by 12 months post-dose observation produced peritoneal sarcoma and lung tumors, respectively.

Mutagenesis

Melphalan has been shown to cause chromatid or chromosome damage in humans. Intramuscular administration of melphalan at 6 and 60 mg/m^2 produced structural aberrations of the chromatid and chromosomes in bone marrow cells of Wistar rats.

Impairment of Fertility

Melphalan causes suppression of ovarian function in premenopausal women, resulting in amenorrhea in a significant number of patients. Reversible and irreversible testicular suppression have also been reported.

Pregnancy

Pregnancy Category D

Melphalan may cause fetal harm when administered to a pregnant woman. While adequate animal studies have not been conducted with IV melphalan, oral (6 to 18 mg/m^2/day for 10 days) and IP (18 mg/m^2) administration in rats was embryolethal and teratogenic. Malformations resulting from melphalan included alterations of the brain (underdevelopment, deformation, meningocele, and encephalocele) and eye (anophthalmia and microphthalmos), reduction of the mandible and tail, as well as hepatocele (exomphaly). There are no adequate and well-controlled studies in pregnant women. If this drug is used during pregnancy, or if the patient becomes pregnant while taking this drug, the patient should be apprised of the potential hazard to the fetus. Women of childbearing potential should be advised to avoid becoming pregnant.

PRECAUTIONS:

General

In all instances where the use of melphalan hydrochloride is considered for chemotherapy, the physician must evaluate the need and usefulness of the drug against the risk of adverse events. Melphalan should be used with extreme caution in patients whose bone marrow reserve may have been compromised by prior irradiation or chemotherapy or whose marrow function is recovering from previous cytotoxic therapy.

Dose reduction should be considered in patients with renal insufficiency receiving IV melphalan. In one trial, increased bone marrow suppression was observed in patients with BUN levels ≥ 30 mg/dL. A 50% reduction in the IV melphalan dose decreased the incidence of severe bone marrow suppression in the latter portion of this study.

Administration of live vaccines to immunocompromised patients should be avoided.

Information for Patients

Patients should be informed that the major acute toxicities of melphalan are related to bone marrow suppression, hypersensitivity reactions, gastrointestinal toxicity, and pulmonary toxicity. The major long-term toxicities are related to infertility and secondary malignancies. Patients should never be allowed to take the drug without close medical supervision and should be advised to consult their physicians if they experience skin rash, signs or symptoms of vasculitis, bleeding, fever, persistent cough, nausea, vomiting, amenorrhea, weight loss, or unusual lumps/masses. Women of childbearing potential should be advised to avoid becoming pregnant.

Laboratory Tests

Periodic complete blood counts with differentials should be performed during the course of treatment with melphalan. At least 1 determination should be obtained prior to each dose. Patients should be observed closely for consequences of bone marrow suppression, which include severe infections, bleeding, and symptomatic anemia (see WARNINGS).

Drug Interactions

The development of severe renal failure has been reported in patients treated with a single dose of IV melphalan followed by standard oral doses of cyclosporine. Cisplatin may affect melphalan kinetics by inducing renal dysfunction and subsequently altering melphalan clearance. IV melphalan may also reduce the threshold for BCNU lung toxicity. When nalidixic acid and IV melphalan are given simultaneously, the incidence of severe hemorrhagic necrotic enterocolitis has been reported to increase in pediatric patients.

Carcinogenesis, Mutagenesis, Impairment of Fertility

(See WARNINGS.)

Pregnancy

Teratogenic Effects

Pregnancy Category D: See WARNINGS.

Nursing Mothers

It is not known whether this drug is excreted in human milk. IV melphalan should not be given to nursing mothers.

Pediatric Use

The safety and effectiveness in pediatric patients have not been established.

Geriatric Use

Clinical studies of melphalan hydrochloride did not include sufficient numbers of subjects aged 65 and over to determine whether they respond differently from younger subjects. Other reported clinical experience has not identified differences in responses between the elderly and younger patients. In general, dose selection for an elderly patient should be cautious, usually starting at the low end of the dosing range, reflecting the greater frequency of decreased hepatic, renal, or cardiac function, and of concomitant disease or other drug therapy.

ADVERSE REACTIONS:

(See OVERDOSAGE.)

The following information on adverse reactions is based on data from both oral and IV administration of melphalan as a single agent, using several different dose schedules for treatment of a wide variety of malignancies.

Hematologic

The most common side effect is bone marrow suppression leading to leukopenia, thrombocytopenia, and anemia. White blood cell count and platelet count nadirs usually occur 2 to 3 weeks after treatment, with recovery in 4 to 5 weeks after treatment. Irreversible bone marrow failure has been reported.

Gastrointestinal

Gastrointestinal disturbances such as nausea and vomiting, diarrhea, and oral ulceration occur infrequently. Hepatic disorders ranging from abnormal liver function tests to clinical manifestations such as hepatitis and jaundice have been reported. Hepatic veno-occlusive disease has been reported.

Hypersensitivity

Acute hypersensitivity reactions including anaphylaxis were reported in 2.4% of 425 patients receiving melphalan hydrochloride for myeloma (see WARNINGS). These reactions were characterized by urticaria, pruritus, edema, skin rashes, and in some patients, tachycardia, bronchospasm, dyspnea, and hypotension. These patients appeared to respond to antihistamine and corticosteroid therapy. If a hypersensitivity reaction occurs, IV or oral melphalan should not be readministered since hypersensitivity reactions have also been reported with oral melphalan. Cardiac arrest has also been reported rarely in association with such reports.

Miscellaneous

Other reported adverse reactions include skin hypersensitivity, skin ulceration at injection site, skin necrosis rarely requiring skin grafting, maculopapular rashes, vasculitis, alopecia, hemolytic anemia, allergic reaction, pulmonary fibrosis (including fatal outcomes), and interstitial pneumonitis. Temporary significant elevation of the blood urea has been seen in the early stages of therapy in patients with renal damage. Subjective and transient sensation of warmth and/or tingling.

OVERDOSAGE:

Overdoses resulting in death have been reported. Overdoses, including doses up to 290 mg/m^2, have produced the following symptoms: severe nausea and vomiting, decreased consciousness, convulsions, muscular paralysis, and cholinomimetic effects. Severe mucositis, stomatitis, colitis, diarrhea, and hemorrhage of the gastrointestinal tract occur at high doses (> 100 mg/m^2). Elevations in liver enzymes and veno-occlusive disease occur infrequently. Significant hyponatremia caused by an associated inappropriate secretion of ADH syndrome has been observed. Nephrotoxicity and adult respiratory distress syndrome have been reported rarely. The principal toxic effect is bone marrow suppression. Hematologic parameters should be closely followed for 3 to 6 weeks. An uncontrolled study suggests that administration of autologous bone marrow or hematopoietic growth factors (i.e., sargramostim, filgrastim) may shorten the period of pancytopenia. General supportive measures together with appropriate blood transfusions and antibiotics should be instituted as deemed necessary by the physician. This drug is not removed from plasma to any significant degree by hemodialysis or hemoperfusion. A pediatric patient survived a 254 mg/m^2 overdose treated with standard supportive care.

DOSAGE AND ADMINISTRATION:

The usual IV dose is 16 mg/m^2. Dosage reduction of up to 50% should be considered in patients with renal insufficiency (BUN ≥ 30 mg/dL) (see PRECAUTIONS, General). The drug is administered as a single infusion over 15 to 20 minutes. Melphalan hydrochloride for injection is administered at 2-week intervals for 4 doses, then, after adequate recovery from toxicity, at 4‑week intervals. Available evidence suggests about one-third to one-half of the patients with multiple myeloma show a favorable response to the drug. Experience with oral melphalan suggests that repeated courses should be given since improvement may continue slowly over many months, and the maximum benefit may be missed if treatment is abandoned prematurely. Dose adjustment on the basis of blood cell counts at the nadir and day of treatment should be considered.

Administration Precautions

As with other toxic compounds, caution should be exercised in handling and preparing the solution of melphalan hydrochloride for injection. Skin reactions associated with accidental exposure may occur. The use of gloves is recommended. If the solution of melphalan hydrochloride contacts the skin or mucosa, immediately wash the skin or mucosa thoroughly with soap and water.

Procedures for proper handling and disposal of anticancer drugs should be considered. Several guidelines on this subject have been published.^1-4 There is no general agreement that all of the procedures recommended in the guidelines are necessary or appropriate.

Parenteral drug products should be visually inspected for particulate matter and discoloration prior to administration whenever solution and container permit. If either occurs, do not use this product.

Care should be taken to avoid possible extravasation of melphalan and in cases of poor peripheral venous access, consideration should be given to use of a central venous line (see WARNINGS).

Preparation for Administration/Stability

1. Melphalan hydrochloride for injection must be reconstituted by rapidly injecting 10 mL of the supplied diluent directly into the vial of lyophilized powder using a sterile needle (20‑gauge or larger needle diameter) and syringe. Immediately shake vial vigorously until a clear solution is obtained. This provides a 5 mg/mL solution of melphalan. Rapid addition of the diluent followed by immediate vigorous shaking is important for proper dissolution.
2. Immediately dilute the dose to be administered in 0.9% Sodium Chloride Injection, USP, to a concentration not greater than 0.45 mg/mL.
3. Administer the diluted product over a minimum of 15 minutes.
4. Complete administration within 60 minutes of reconstitution.

The time between reconstitution/dilution and administration of melphalan hydrochloride should be kept to a minimum because reconstituted and diluted solutions of melphalan hydrochloride are unstable. Over as short a time as 30 minutes, a citrate derivative of melphalan has been detected in reconstituted material from the reaction of melphalan hydrochloride with Sterile Diluent for melphalan hydrochloride. Upon further dilution with saline, nearly 1% label strength of melphalan hydrolyzes every 10 minutes.

A precipitate forms if the reconstituted solution is stored at 5°C. DO NOT REFRIGERATE THE RECONSTITUTED PRODUCT.

HOW SUPPLIED:

Melphalan hydrochloride for injection is supplied as follows:

Product No. | NDC No. | Strength
762020 | 63323-760-20 | 50 mg per vial | One carton containing one single use clear glass vial of freeze-dried melphalan hydrochloride equivalent to 50 mg melphalan and one 10 mL clear glass vial of sterile diluent.

Store at 20° to 25°C (68° to 77°F) [see USP Controlled Room Temperature] and protect from light.

The container closure is not made with natural rubber latex.

REFERENCES:

1. NIOSH Alert: Preventing Occupational Exposures to Antineoplastic and Other Hazardous Drugs in Healthcare Settings. U.S. Department of Health and Human Services, Public Health Service. Centers for Disease Control and Prevention, National Institute for Occupational Safety and Health, DHHS (NIOSH) Publication No. 2004-165.
2. OSHA Technical Manual, TED 1-0.15A, Section VI: Chapter 2. Controlling Occupational Exposure to Hazardous Drugs. OSHA, 1999. http://www.osha.gov/dts/osta/otm/otm/_vi/otm_vi_2.html
3. American Society of Health-System Pharmacists. (2006) ASHP Guidelines on Handling Hazardous Drugs. Am J Health-Syst Pharm. 2006;63: 1172-1193.
4. Polovich M, White JM, Kelleher LO (eds.) 2005. Chemotherapy and Biotherapy Guidelines and Recommendations for Practice. (2nd ed.) Pittsburgh, PA: Oncology Nursing Society.

Lake Zurich, IL 60047

www.fresenius-kabi.us

451229

Issued: August 2016

PACKAGE LABEL

PACKAGE LABEL - PRINCIPAL DISPLAY - Melphalan Hydrochloride Kit - Diluent Vial Label Panel
Sterile Diluent for Melphalan Hydrochloride for Injection
For drug diluent use only.
10 mL Rx only

PACKAGE LABEL - PRINCIPAL DISPLAY - Melphalan Hydrochloride Kit - Melphalan 50 mg Vial Label Panel
Melphalan Hydrochloride for Injection
50 mg* per vial
For intravenous infusion.
Cytotoxic agent.
Drug product will contain 5% v/v alcohol content upon reconstitution with accompanying diluent.
Single Use Vial Rx only

PACKAGE LABEL - PRINCIPAL DISPLAY - Melphalan Hydrochloride Kit - Melphalan 50 mg Vial Carton Panel
Melphalan Hydrochloride for Injection NDC 63323-760-20
50 mg* per vial
For intravenous infusion.
Cytotoxic agent.
Single Use Vials
Rx only